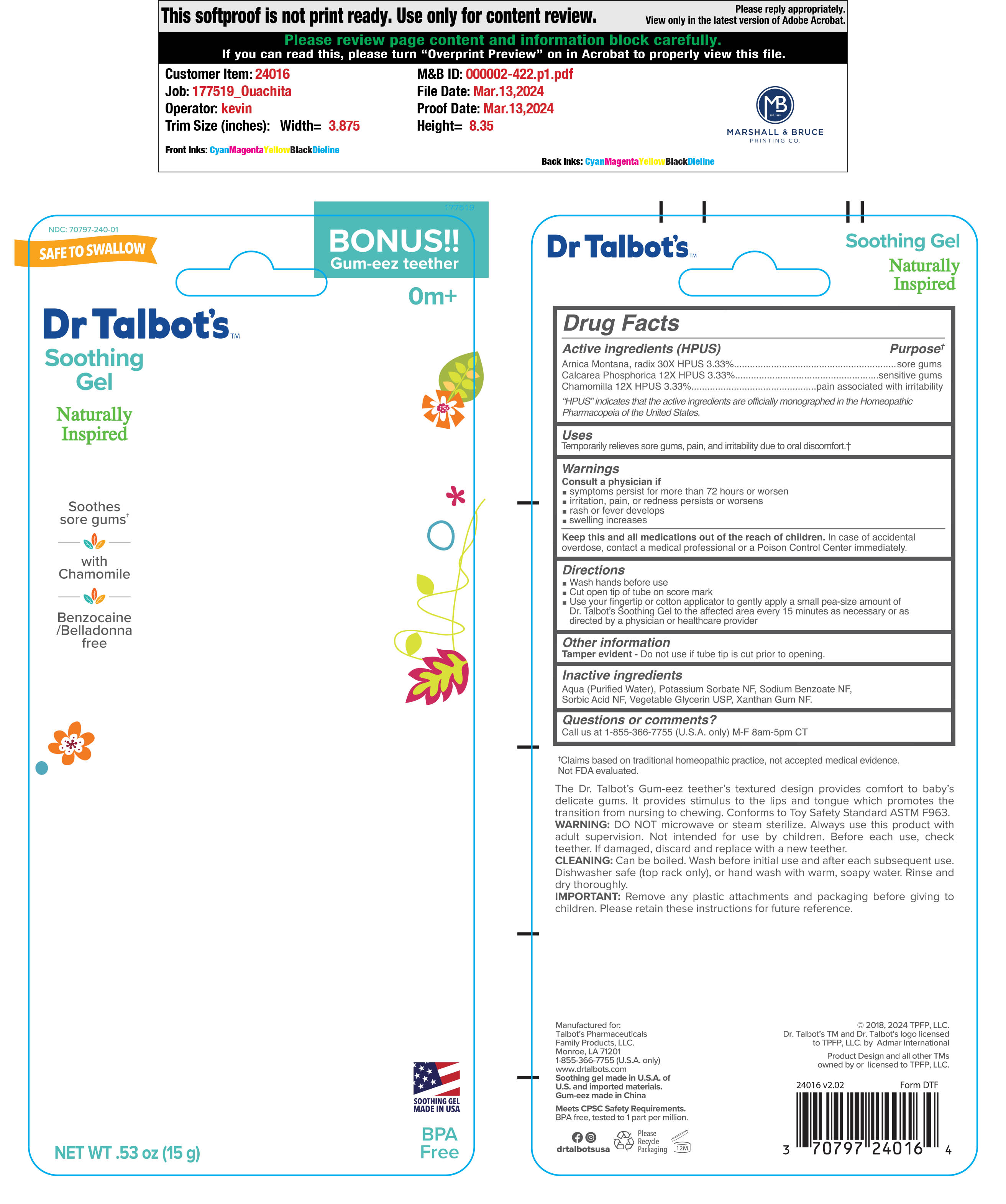 DRUG LABEL: Nuby Soothing Gel
NDC: 85182-240 | Form: GEL
Manufacturer: NINGBO RAFFINI IMPORTS & EXPORTS CO LTD
Category: homeopathic | Type: HUMAN OTC DRUG LABEL
Date: 20250121

ACTIVE INGREDIENTS: TRIBASIC CALCIUM PHOSPHATE 12 [hp_X]/15 g; MATRICARIA RECUTITA 12 [hp_X]/15 g; ARNICA MONTANA ROOT 30 [hp_X]/15 g
INACTIVE INGREDIENTS: SORBIC ACID; SODIUM BENZOATE; WATER; XANTHAN GUM; POTASSIUM SORBATE; GLYCERIN

ACTIVE INGREDIENT

- Arnica, radix 30X HPUS 3.33 %
- Calcarea phosphorica 12XHPUS 3.33 %
- Chamomilla 12X HPUS 3.33 %

INACTIVE INGREDIENT

- Aqua (Purified Water)
- Potassium Sorbate NF
- Sodium Benzoate NF
- Sorbic Acid NF
- Vegetable Glycerin USP
- Xantham Gum NF

PURPOSE

Temporarily relieves sore gums, pain, and irritability due to oral discomfort.

WARNINGS

Counsult a Physician if

- symptoms persist for more than 72 hours or worsen
- irritation, pain, or redness persits or worsen
- rash or fever develops
- swelling increases

- Wash hands before use
- Cut open tip of tube on score mark
- Use your fingertip or cotton applicator to gently apply a small pea-sized maount of Dr. Talbot's Soothing Gel to the affected area 15 miniutes as neccassary or as directed by a physician or health provider

KEEP OUT OF REACH OF CHILDREN

Keep this and all medication out of the reach of children.

In case of accidental overdose, contact a medical professional or a Poison Control immidiately.

QUESTIONS

Call us at 1-855-366-7755 (U.S.A. only) M-F 8 am - 5 pm CT

OTHER SAFETY INFORMATION

Tamper evident - Do not use if tube tip is cut prior to opening

PACKAGE LABEL

DR. Talbot's

Soothing Gel

Naturally Inspired

Soothes sore Gums

with Chamomile

Benzocaine/Belladonna free